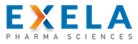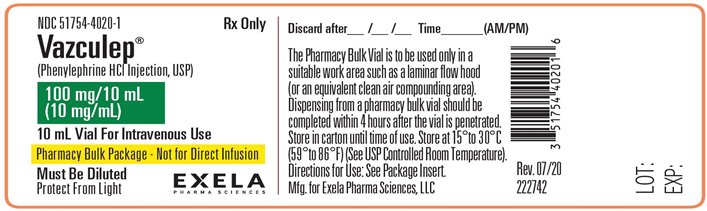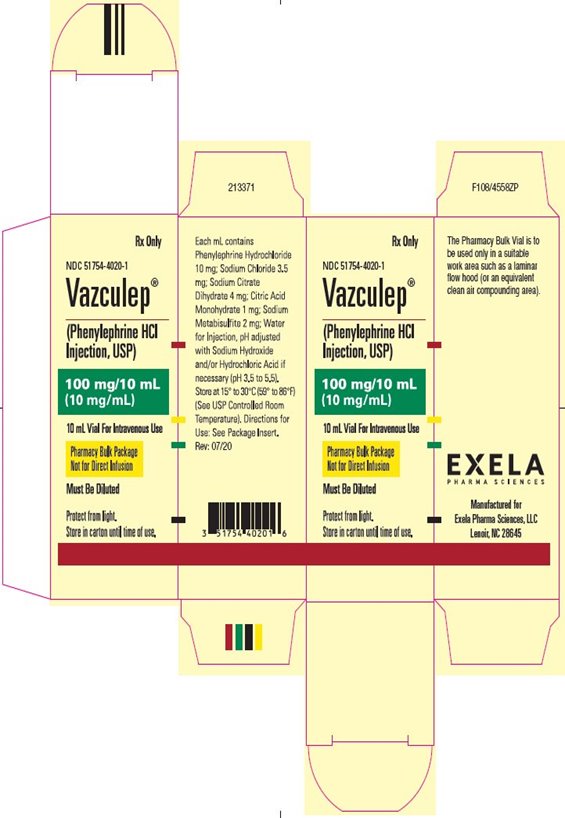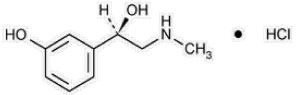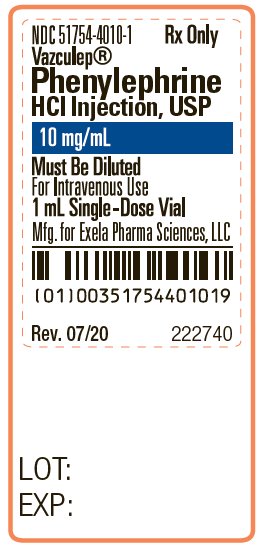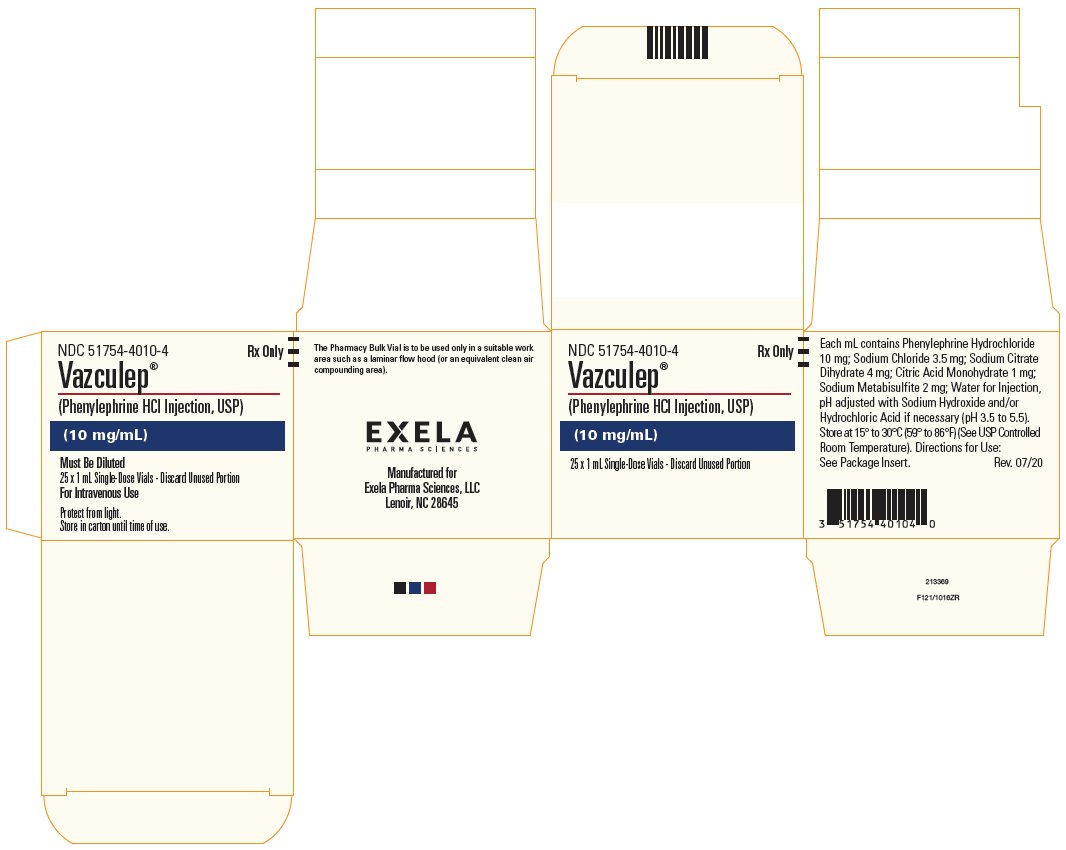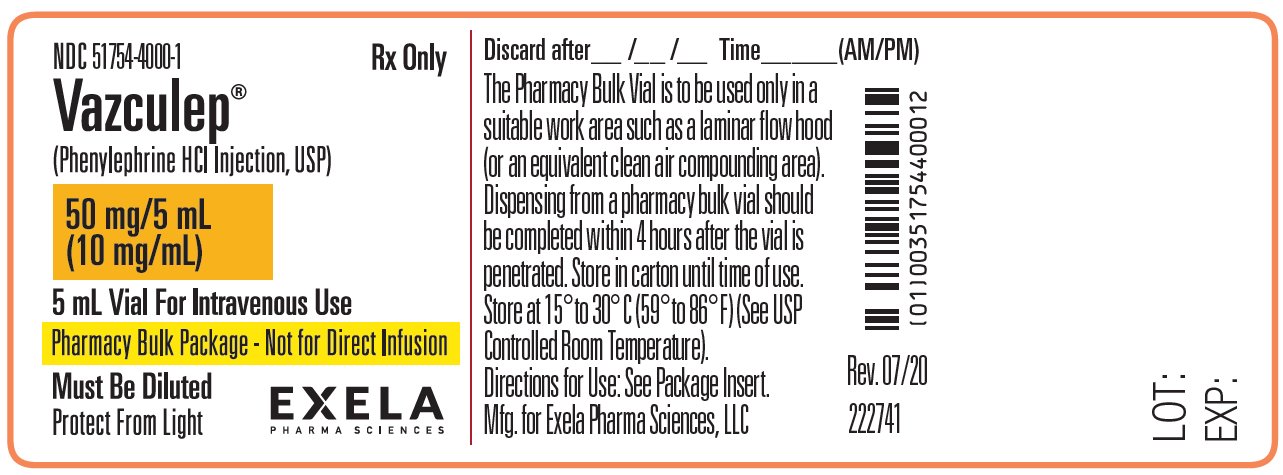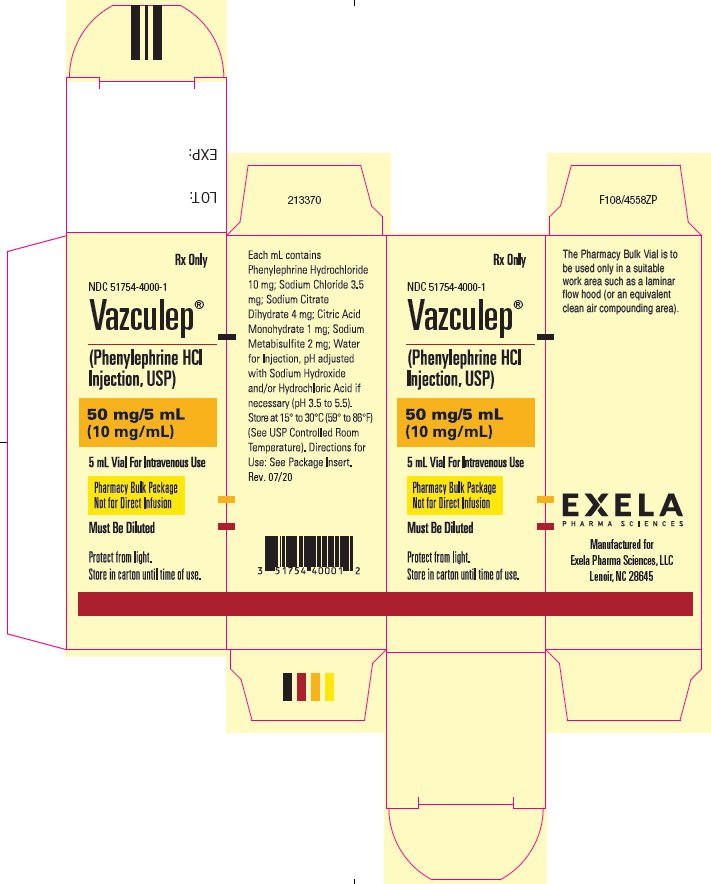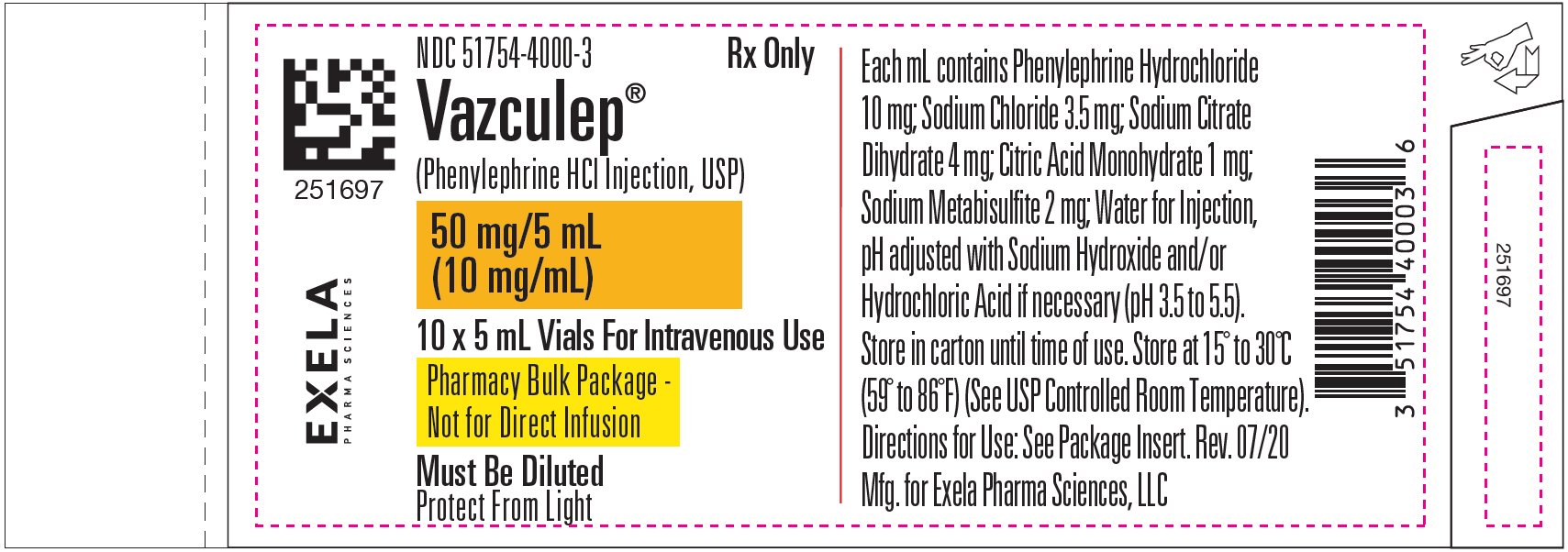 DRUG LABEL: Vazculep
NDC: 51754-4010 | Form: INJECTION
Manufacturer: Exela Phrama Sciences, LLC
Category: prescription | Type: HUMAN PRESCRIPTION DRUG LABEL
Date: 20210326

ACTIVE INGREDIENTS: PHENYLEPHRINE HYDROCHLORIDE 10 mg/1 mL
INACTIVE INGREDIENTS: SODIUM CHLORIDE 3.5 mg/1 mL; TRISODIUM CITRATE DIHYDRATE 4 mg/1 mL; CITRIC ACID MONOHYDRATE 1 mg/1 mL; SODIUM METABISULFITE 2 mg/1 mL; WATER; SODIUM HYDROXIDE; HYDROCHLORIC ACID

HIGHLIGHTS OF PRESCRIBING INFORMATION

These highlights do not include all the information needed to use
VAZCULEP™ safely and effectively. See full prescribing information for VAZCULEP.
VAZCULEP (phenylephrine hydrochloride) Injection for intravenous use
Initial U.S. Approval: 1954

1 INDICATIONS AND USAGE

VAZCULEP injection is an α-1 adrenergic receptor agonist indicated for the treatment of clinically important hypotension resulting primarily from vasodilation in the setting of anesthesia. (1)

2 DOSAGE AND ADMINISTRATION

VAZCULEP injection is injected intravenously either as a bolus or in a dilute solution as a continuous infusion. Dilute before administration. (2)

Dosing for treatment of hypotension during anesthesia

- Bolus intravenous injection: 40 mcg to 100 mcg every 1 to 2 minutes as needed, not to exceed 200 mcg. (2)
- Intravenous infusion: 10 mcg/min to 35 mcg/min, titrating to effect, not to exceed 200 mcg/min. (2)

Adjust the dose according to the pressor response (i.e., titrate to effect). (2)

3 DOSAGE FORMS AND STRENGTHS

- Injection (3)
- 1 mL single-dose vials containing 10 mg phenylephrine hydrochloride (10 mg/mL) (3)
- 5 mL pharmacy bulk package vials containing 50 mg phenylephrine hydrochloride (10 mg/mL) (3)
- 10 mL pharmacy bulk package vials containing 100 mg phenylephrine hydrochloride (10 mg/mL) (3)

4 CONTRAINDICATIONS

None (4)

5 WARNINGS AND PRECAUTIONS

Exacerbation of Angina, Heart Failure, or Pulmonary Arterial Hypertension: VAZCULEP can precipitate angina in patients with severe arteriosclerosis or history of angina, exacerbate underlying heart failure, and increase pulmonary arterial pressure. (5.1)

Peripheral and Visceral Ischemia: VAZCULEP can cause excessive peripheral and visceral vasoconstriction and ischemia to vital organs. (5.2)

Skin and Subcutaneous Necrosis: Extravasation during intravenous administration may cause necrosis or sloughing of tissue. (5.3)

Bradycardia: VAZCULEP can cause severe bradycardia and decreased cardiac output. (5.4)

6 ADVERSE REACTIONS

Most common adverse reactions during treatment: nausea, vomiting, and headache. (6)

To report SUSPECTED ADVERSE REACTIONS, contact Exela Pharma Sciences, LLC at 1-888-451-4321 or FDA at 1-800-FDA-1088 or www.fda.gov/medwatch.

7 DRUG INTERACTIONS

- Agonistic effects (increase in VAZCULEP blood pressure effect) can occur with monoamine oxidase inhibitors (MAOI), oxytocin and oxytocic drugs, tricyclic antidepressants, angiotensin and aldosterone, atropine, steroids, norepinephrine transporter inhibitors, ergot alkaloids (7.1)
- Antagonistic effects (decrease in VAZCULEP blood pressure effect) can occur with α-adrenergic antagonists, phosphodiesterase Type 5 inhibitors, mixed α- and β-receptor antagonists, calcium channel blockers, benzodiazepines and ACE inhibitors, centrally acting sympatholytic agents (7.2)

FULL PRESCRIBING INFORMATION

1 INDICATIONS AND USAGE

VAZCULEP is indicated for the treatment of clinically important hypotension resulting primarily from vasodilation in the setting of anesthesia.

2 DOSAGE AND ADMINISTRATION

2.1 General Dosage and Administration Instructions

VAZCULEP must be diluted before administration as an intravenous bolus or continuous intravenous infusion to achieve the desired concentration:

- Bolus: Dilute with normal saline or 5% dextrose in water.
- Continuous infusion: Dilute with normal saline or 5% dextrose in water.

Parenteral drug products should be inspected visually for particulate matter and discoloration prior to administration. Do not use if the solution is colored or cloudy, or if it contains particulate matter. The diluted solution should not be held for more than 4 hours at room temperature or for more than 24 hours under refrigerated conditions. Discard any unused portion.

During VAZCULEP administration:

- Correct intravascular volume depletion.
- Correct acidosis. Acidosis may reduce the effectiveness of phenylephrine.

2.2 Dosing for Treatment of Hypotension during Anesthesia

The following are the recommended dosages for the treatment of hypotension during anesthesia.

- The recommended initial dose is 40 to 100 mcg administered by intravenous bolus. Additional boluses may be administered every 1 to 2 minutes as needed; not to exceed a total dosage of 200 mcg.
- If blood pressure is below the target goal, start a continuous intravenous infusion with an infusion rate of 10 to 35 mcg/minute; not to exceed 200 mcg/minute.
- Adjust dosage according to the blood pressure goal.

2.3 Prepare a 100 mcg/mL Solution for Bolus Intravenous Administration

For bolus intravenous administration, prepare a solution containing a final concentration of 100 mcg/mL of VAZCULEP:

- Withdraw 10 mg (1 mL of 10 mg/mL) of VAZCULEP and dilute with 99 mL of 5% Dextrose Injection, USP or 0.9% Sodium Chloride Injection, USP.
- Withdraw an appropriate dose from the 100 mcg/mL solution prior to bolus intravenous administration.

2.4 Prepare a Solution for Continuous Intravenous Administration

For continuous intravenous infusion, prepare a solution containing a final concentration of 20 mcg/mL of VAZCULEP in 5% Dextrose Injection, USP or 0.9% Sodium Chloride Injection, USP:

- Withdraw 10 mg (1 mL of 10 mg/mL) of VAZCULEP and dilute with 500 mL of 5% Dextrose Injection, USP or 0.9% Sodium Chloride Injection, USP.

2.5 Directions for Dispensing from Pharmacy Bulk Vial

The Pharmacy Bulk Vial is intended for dispensing of single doses to multiple patients in a pharmacy admixture program and is restricted to the preparation of admixtures for infusion. Each closure shall be penetrated only one time with a suitable sterile transfer device or dispensing set that allows measured dispensing of the contents. The Pharmacy Bulk Vial is to be used only in a suitable work area such as a laminar flow hood (or an equivalent clean air compounding area). Dispensing from a pharmacy bulk vial should be completed within 4 hours after the vial is penetrated.

3 DOSAGE FORMS AND STRENGTHS

VAZCULEP (phenylephrine hydrochloride) Injection, 10 mg/mL, for intravenous use, is available in three vial sizes:

- Injection: 10 mg/mL as a clear, colorless solution in a single-dose 1 mL vial (10 mg of phenylephrine hydrochloride per vial)
- Injection: 10 mg/mL as a clear, colorless solution in Pharmacy Bulk Package 5 mL vial (50 mg of phenylephrine hydrochloride per vial) that will provide five 1 mL single doses
- Injection: 10 mg/mL as a clear, colorless solution in Pharmacy Bulk Package 10 mL vial (100 mg of phenylephrine hydrochloride per vial) that will provide ten 1 mL single doses

4 CONTRAINDICATIONS

None

5 WARNINGS AND PRECAUTIONS

5.1 Exacerbation of Angina, Heart Failure, or Pulmonary Arterial Hypertension

Because of its increasing blood pressure effects, VAZCULEP can precipitate angina in patients with severe arteriosclerosis or history of angina, exacerbate underlying heart failure, and increase pulmonary arterial pressure.

5.2 Peripheral and Visceral Ischemia

VAZCULEP can cause excessive peripheral and visceral vasoconstriction and ischemia to vital organs, particularly in patients with extensive peripheral vascular disease.

5.3 Skin and Subcutaneous Necrosis

Extravasation of VAZCULEP can cause necrosis or sloughing of tissue. The infusion site should be checked for free flow. Care should be taken to avoid extravasation of VAZCULEP.

5.4 Bradycardia

VAZCULEP can cause severe bradycardia and decreased cardiac output.

5.5 Allergic Reactions

VAZCULEP contains sodium metabisulfite, a sulfite that may cause allergic-type reactions, including anaphylactic symptoms and life-threatening or less severe asthmatic episodes in certain susceptible people. The overall prevalence of sulfite sensitivity in the general population is unknown and probably low. Sulfite sensitivity is seen more frequently in asthmatic than in nonasthmatic people.

5.6 Renal Toxicity

VAZCULEP can increase the need for renal replacement therapy in patients with septic shock. Monitor renal function.

5.7 Risk of Augmented Pressor Effect in Patients with Autonomic Dysfunction

The increasing blood pressure response to adrenergic drugs, including VAZCULEP, can be increased in patients with autonomic dysfunction, as may occur with spinal cord injuries.

5.8 Pressor Effect with Concomitant Oxytocic Drugs

Oxytocic drugs potentiate the increasing blood pressure effect of sympathomimetic pressor amines including VAZCULEP [see Drug Interactions (7.1)], with the potential for hemorrhagic stroke.

6 ADVERSE REACTIONS

Adverse reactions to VAZCULEP are primarily attributable to excessive pharmacologic activity. Adverse reactions reported in published clinical studies, observational trials, and case reports of VAZCULEP are listed below by body system. Because these reactions are reported voluntarily from a population of uncertain size, it is not always possible to estimate their frequency reliably or to establish a causal relationship to drug exposure.

Cardiac disorders: Reflex bradycardia, lowered cardiac output, ischemia, hypertension, arrhythmias

Gastrointestinal disorders: Epigastric pain, vomiting, nausea

Nervous system disorders: Headache, blurred vision, neck pain, tremors

Vascular disorders: Hypertensive crisis

Respiratory, Thoracic and Mediastinal Disorders: Dyspnea

Skin and subcutaneous tissue disorders: Pruritis

7 DRUG INTERACTIONS

7.1 Interactions that Augment Pressor Effect

The increasing blood pressure effect of VAZCULEP is increased in patients receiving:

- Monoamine oxidase inhibitors (MAOI)
- Oxytocin and oxytocic drugs
- Tricyclic antidepressants
- Angiotensin, aldosterone
- Atropine
- Steroids, such as hydrocortisone
- Norepinephrine transporter inhibitors, such as atomoxetine
- Ergot alkaloids, such as methylergonovine maleate

7.2 Interactions that Antagonize the Pressor Effect

The increasing blood pressure effect of VAZCULEP is decreased in patients receiving:

- α-adrenergic antagonists
- Phosphodiesterase Type 5 inhibitors
- Mixed α- and β-receptor antagonists
- Calcium channel blockers, such as nifedipine
- Benzodiazepines
- ACE inhibitors
- Centrally acting sympatholytic agents, such as reserpine, guanfacine

8 USE IN SPECIFIC POPULATIONS

8.1 Pregnancy

Risk Summary

Data from randomized controlled trials and meta-analyses with phenylephrine hydrochloride injection use in pregnant women during Cesarean section have not established a drug-associated risk of major birth defects and miscarriage. These studies have not identified an adverse effect on maternal outcomes or infant Apgar scores [see Data]. There are no data on the use of phenylephrine during the first or second trimester. In animal reproduction and development studies in normotensive animals, evidence of fetal malformations was noted when phenylephrine was administered during organogenesis via a 1-hour infusion at 1.2 times the human daily dose (HDD) of 10 mg/60 kg/day. Decreased pup weights were noted in offspring of pregnant rats treated with 2.9 times the HDD [See Data]. The estimated background risk of major birth defects and miscarriage for the indicated population are unknown. All pregnancies have a background risk of birth defect, loss, or other adverse outcomes. In the U.S. general population, the estimated background risk of major birth defects and miscarriage in clinically recognized pregnancies is 2-4% and 15-20%, respectively.

Clinical Considerations

Disease-Associated Maternal and/or Embryofetal Risk

Untreated hypotension associated with spinal anesthesia for Cesarean section is associated with an increase in maternal nausea and vomiting. A sustained decrease in uterine blood flow due to maternal hypotension may result in fetal bradycardia and acidosis.

Data

Human Data

Published randomized controlled trials over several decades, which compared the use of phenylephrine injection to other similar agents in pregnant women during Cesarean section, have not identified adverse maternal or infant outcomes. At recommended doses, phenylephrine does not appear to affect fetal heart rate or fetal heart rate variability to a significant degree.

There are no studies on the safety of phenylephrine injection exposure during the period of organogenesis, and therefore, it is not possible to draw any conclusions on the risk of birth defects following exposure to phenylephrine injection during pregnancy. In addition, there are no data on the risk of miscarriage following fetal exposure to phenylephrine injection.

Animal Data

No clear malformations or fetal toxicity were reported when normotensive pregnant rabbits were treated with phenylephrine via continuous intravenous infusion over 1 hour (0.5 mg/kg/day; approximately equivalent to a HDD based on body surface area) from Gestation Day 7 to 19. At this dose, which demonstrated no maternal toxicity, there was evidence of developmental delay (altered ossification of sternebra).

In a non-GLP dose range-finding study in normotensive pregnant rabbits, fetal lethality and cranial, paw, and limb malformations were noted following treatment with 1.2 mg/kg/day of phenylephrine via continuous intravenous infusion over 1 hour (2.3-times the HDD). This dose was clearly maternally toxic (increased mortality and significant body weight loss). An increase in the incidence of limb malformation (hyperextension of the forepaw) coincident with high fetal mortality was noted in a single litter at 0.6 mg/kg/day (1.2-times the HDD) in the absence of maternal toxicity.

No malformations or embryo-fetal toxicity were reported when normotensive pregnant rats were treated with up to 3 mg/kg/day phenylephrine via continuous intravenous infusion over 1 hour (2.9-times the HDD) from Gestation Day 6 to 17. This dose was associated with some maternal toxicity (decreased food consumption and body weights).

Decreased pup weights were reported in a pre- and postnatal development toxicity study in which normotensive pregnant rats were administered phenylephrine via continuous intravenous infusion over 1 hour (0.3, 1.0, or 3.0 mg/kg/day; 0.29, 1, or 2.9 times the HDD) from Gestation Day 6 through Lactation Day 21). No adverse effects on growth and development (learning and memory, sexual development, and fertility) were noted in the offspring of pregnant rats at any dose tested. Maternal toxicities (mortality late in gestation and during lactation period, decreased food consumption and body weight) occurred at 1 and 3 mg/kg/day of phenylephrine (equivalent to and 2.9 times the HDD, respectively).

8.2 Lactation

Risk Summary

There are no data on the presence of phenylephrine hydrochloride injection or its metabolite in human or animal milk, the effects on the breastfed infant, or the effects on milk production. The developmental and health benefits of breastfeeding should be considered along with the mother’s clinical need for VAZCULEP and any potential adverse effects on the breastfed infant from VAZCULEP or from the underlying maternal condition.

8.4 Pediatric Use

Safety and effectiveness in pediatric patients have not been established.

8.5 Geriatric Use

Clinical studies of phenylephrine did not include sufficient numbers of subjects aged 65 and over to determine whether they respond differently from younger subjects. Other reported clinical experience has not identified differences in responses between the elderly and younger patients. In general, dose selection for an elderly patient should be cautious, usually starting at the low end of the dosing range, reflecting the greater frequency of decreased hepatic, renal, or cardiac function, and of concomitant disease or other drug therapy.

8.6 Hepatic Impairment

In patients with liver cirrhosis [Child Pugh Class B and Class C], dose-response data indicate decreased responsiveness to phenylephrine. Start dosing in the recommended dose range, but more phenylephrine may be needed in this population.

8.7 Renal Impairment

In patients with end stage renal disease (ESRD), dose-response data indicate increased responsiveness to phenylephrine. Consider starting at the lower end of the recommended dose range, and adjusting dose based on the target blood pressure goal.

10 OVERDOSAGE

Overdose of VAZCULEP can cause a rapid rise in blood pressure. Symptoms of overdose include headache, vomiting, hypertension, reflex bradycardia, a sensation of fullness in the head, tingling of the extremities, and cardiac arrhythmias including ventricular extrasystoles and ventricular tachycardia.

11 DESCRIPTION

Phenylephrine is an α-1 adrenergic receptor agonist. VAZCULEP (phenylephrine hydrochloride) Injection, 10 mg/mL, is a clear, colorless, sterile, nonpyrogenic solution for intravenous use. It must be diluted before administration as an intravenous bolus or continuous intravenous infusion. The chemical name of phenylephrine hydrochloride is (-)-m-hydroxy-α-[(methylamino)methyl]benzyl alcohol hydrochloride and is chemically designated as C9H14ClNO2 with a molecular weight of 203.66 g/mol. Its structural formula is depicted below:

Phenylephrine hydrochloride is soluble in water and ethanol, and insoluble in chloroform and ethyl ether. VAZCULEP (phenylephrine hydrochloride) Injection, 10 mg/mL, is sensitive to light. Each mL contains: phenylephrine hydrochloride 10 mg, sodium chloride 3.5 mg, sodium citrate dihydrate 4 mg, citric acid monohydrate 1 mg, and sodium metabisulfite 2 mg in water for injection. The pH is adjusted with sodium hydroxide and/or hydrochloric acid if necessary. The pH range is 3.5 to 5.5.

12 CLINICAL PHARMACOLOGY

12.1 Mechanism of Action

Phenylephrine hydrochloride is an α-1 adrenergic receptor agonist.

12.2 Pharmacodynamics

Interaction of phenylephrine with α-1 adrenergic receptors on vascular smooth muscle cells causes activation of the cells and results in vasoconstriction. Following phenylephrine hydrochloride intravenous administration, increases in systolic and diastolic blood pressures, mean arterial blood pressure, and total peripheral vascular resistance are observed. The onset of blood pressure increase following an intravenous bolus phenylephrine hydrochloride administration is rapid, typically within minutes. As blood pressure increases following intravenous administration, vagal activity also increases, resulting in reflex bradycardia. Phenylephrine has activity on most vascular beds, including renal, pulmonary, and splanchnic arteries.

12.3 Pharmacokinetics

Following an intravenous infusion of phenylephrine hydrochloride, the observed effective half-life was approximately 5 minutes. The steady-state volume of distribution of approximately 340 L suggests a high distribution into organs and peripheral tissues. The average total serum clearance is approximately 2100 mL/min. The observed phenylephrine plasma terminal elimination half-life was 2.5 hours.

Phenylephrine is metabolized primarily by monoamine oxidase and sulfotransferase. After intravenous administration of radiolabeled phenylephrine, approximately 80% of the total dose was eliminated within first 12 h; and approximately 86% of the total dose was recovered in the urine within 48 h. The excreted unchanged parent drug was 16% of the total dose in the urine at 48 h post intravenous administration. There are two major metabolites, with approximately 57 and 8% of the total dose excreted as m-hydroxymandelic acid and sulfate conjugates, respectively. The metabolites are considered not pharmacologically active.

13 NONCLINICAL TOXICOLOGY

13.1 Carcinogenesis, Mutagenesis, Impairment of Fertility

Carcinogenesis

Long-term animal studies that evaluated the carcinogenic potential of orally administered phenylephrine hydrochloride in F344/N rats and B6C3F1 mice were completed by the National Toxicology Program using the dietary route of administration. There was no evidence of carcinogenicity in mice administered approximately 270 mg/kg/day (131 times the human daily dose (HDD) of 10 mg/60 kg/day based on body surface area) or rats administered approximately 50 mg/kg/day (48 times HDD) based on body surface area comparisons.

Mutagenesis

Phenylephrine hydrochloride tested negative in the in vitro bacterial reverse mutation assay (S.typhimurium strains TA98, TA100, TA1535 and TA1537), the in vitro chromosomal aberrations assay, the in vitro sister chromatid exchange assay, and the in vivo rat micronucleus assay. Positive results were reported in only one of two replicates of the in vitro mouse lymphoma assay.

Impairment of Fertility

Phenylephrine did not impair mating, fertility, or reproductive outcome in normotensive male rats treated with 3 mg/kg/day phenylephrine via continuous intravenous infusion over 1 hour (2.9 times the HDD) for 28 days prior to mating and for a minimum of 63 days prior to sacrifice and female rats treated with the same dosing regimen for 14 days prior to mating and through Gestation Day 6. This dose was associated with increased mortality in both male and female rats and decreased body weight gain in treated males. There were decreased caudal sperm density and increased abnormal sperm reported in males treated with 3 mg/kg/day phenylephrine (2.9 times the HDD).

14 CLINICAL STUDIES

The evidence for the efficacy of VAZCULEP is derived from studies of phenylephrine hydrochloride in the published literature. The literature support includes 16 studies evaluating the use of intravenous phenylephrine to treat hypotension during anesthesia. The 16 studies include 9 studies where phenylephrine was used in low-risk (ASA 1 and 2) pregnant women undergoing neuraxial anesthesia during Cesarean delivery, 6 studies in non-obstetric surgery under general anesthesia, and 1 study in non-obstetric surgery under combined general and neuraxial anesthesia. Phenylephrine has been shown to raise systolic and mean blood pressure when administered either as a bolus dose or by continuous infusion following the development of hypotension during anesthesia.

16 HOW SUPPLIED/STORAGE AND HANDLING

VAZCULEP (phenylephrine hydrochloride) Injection, 10 mg/mL, is a clear, colorless solution supplied as follows:

NDC No. | Strength | How Supplied
51754-4010-4 | 10 mg/mL | 1 mL vial; for single use (supplied in packages of 25)
51754-4000-3 | 10 mg/mL | 5 mL vial; Pharmacy Bulk Package (supplied in packages of 10)
51754-4020-1 | 10 mg/mL | 10 mL vial; Pharmacy Bulk Package (supplied as a single unit)

Vial stoppers are not manufactured with natural rubber latex. Store VAZCULEP (phenylephrine hydrochloride) Injection, 10 mg/mL at 20°C to 25°C (68°F to 77°F), excursions permitted to 15°C to 30°C (59°F to 86°F) [see USP Controlled Room Temperature]. Protect from light. Store in carton until time of use. The 1 mL vials are for single use only; the 5 and 10 mL vials are pharmacy bulk packages.

The diluted solution should not be held for more than 4 hours at room temperature or for more than 24 hours under refrigerated conditions. Discard any unused portion.

17 PATIENT COUNSELING INFORMATION

If applicable, inform patient, family member, or caregiver that certain medical conditions and medications might influence how VAZCULEP (phenylephrine hydrochloride) Injection works.

Manufactured for:

Exela Pharma Sciences, LLC

Lenoir, NC 28613

Package Label - Principal Display Panel - 1 mL Vial - Container Label

NDC 51754-4010-1 Rx Only

Vazculep

Phenylephrine

HCl Injection, USP

10 mg/mL

Must Be Diluted

For Intravenous Use

1 mL Single Dose Vial

Package Label - Principal Display Panel - 1 mL Vial - Carton Label

NDC 51754-4010-4 Rx Only

Vazculep

(Phenylephrine HCl Injection, USP)

25 x 1 mL Single Dose Vials – Discard Unused Portion

For Intravenous Use

Protect from light

Store in carton until time of use

Package Label - Principal Display Panel - 5 mL Vial - Container Label

NDC 51754-4000-1 Rx Only

Vazculep

(Phenylephrine HCl Injection, USP)

50 mg/5 mL

(10 mg/mL)

5 mL Vial For Intravenous Use

Pharmacy Bulk Package – Not for Direct Infusion

Must Be Diluted

Protect From Light

Package Label - Principal Display Panel - 5 mL Vial - Carton Label

NDC 51754-4000-1 Rx Only

Vazculep

(Phenylephrine HCl

Injection, USP)

50 mg/5 mL

(10 mg/mL)

5 mL Vial For Intravenous Use

Pharmacy Bulk Package

Not for Direct Infusion

Must Be Diluted

Protect from of light

Store in carton until time of use

Package Label - Principal Display Panel - 5 mL Vial - Extended Content Label

NDC 51754-4000-3 Rx Only

Vazculep

(Phenylephrine HCl Injection, USP)

50 mg/5 mL

(10 mg/mL)

10 x 5 mL Vials For Intravenous Use

Pharmacy Bulk Package –

Not for Direct Infusion

Must Be Diluted

Protect From Light

PACKAGE/LABEL PRINCIPAL DISPLAY PANEL-10 mL Vial-Container Label

NDC 51754-4020-1 Rx Only

Vazculep

(Phenylephrine HCl Injection, USP)

100 mg/10 mL

(10 mg/mL)

10 mL Vial For Intravenous Use

Pharmacy Bulk Package – Not for Direct Infusion

Must Be Diluted

Protect From Light

PACKAGE/LABEL PRINCIPAL DISPLAY PANEL-10 mL Vial - Carton Label

NDC 51754-4020-1 Rx Only

Vazculep

(Phenylephrine HCl

Injection, USP)

100 mg/10 mL

(10 mg/mL)

10 mL Vial For Intravenous Use

Pharmacy Bulk Package

Not for Direct Infusion

Must Be Diluted

Protect from of light

Store in carton until time of use